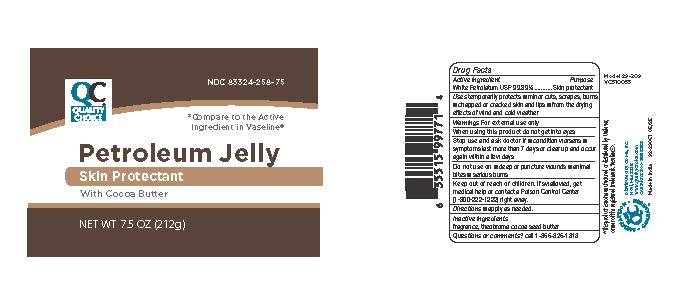 DRUG LABEL: Petroleum with Cocoa
NDC: 83324-258 | Form: JELLY
Manufacturer: QUALITY CHOICE (Chain Drug Marketing Association)
Category: otc | Type: HUMAN OTC DRUG LABEL
Date: 20251113

ACTIVE INGREDIENTS: PETROLATUM 99.89 g/100 g
INACTIVE INGREDIENTS: COCOA BUTTER

Quality Choice Petrolatum Jelly with Cocoa Butter

Warning

For External Use Only

Active Ingredient

Name Purpose

White Petrolatum 99.89% USP .............................. Skin Protectant

Inactive Ingredients

fragrance, theobroma cocoa seed butter

Purpose

Skin Protectant

Keep out of the reach of children

If swallowed, get medical help or contact a Poison Control Center (1-800-222-1222)right away

Uses

Temporarily Protects:

minor cuts, scrapes, burns and helps relieve chapped or cracked skin and lips from the drying effects of wind and cold weather

Do not use

■ deep or puncture wounds ■ animal bites ■ serious burns

Dosage

Applied as needed.